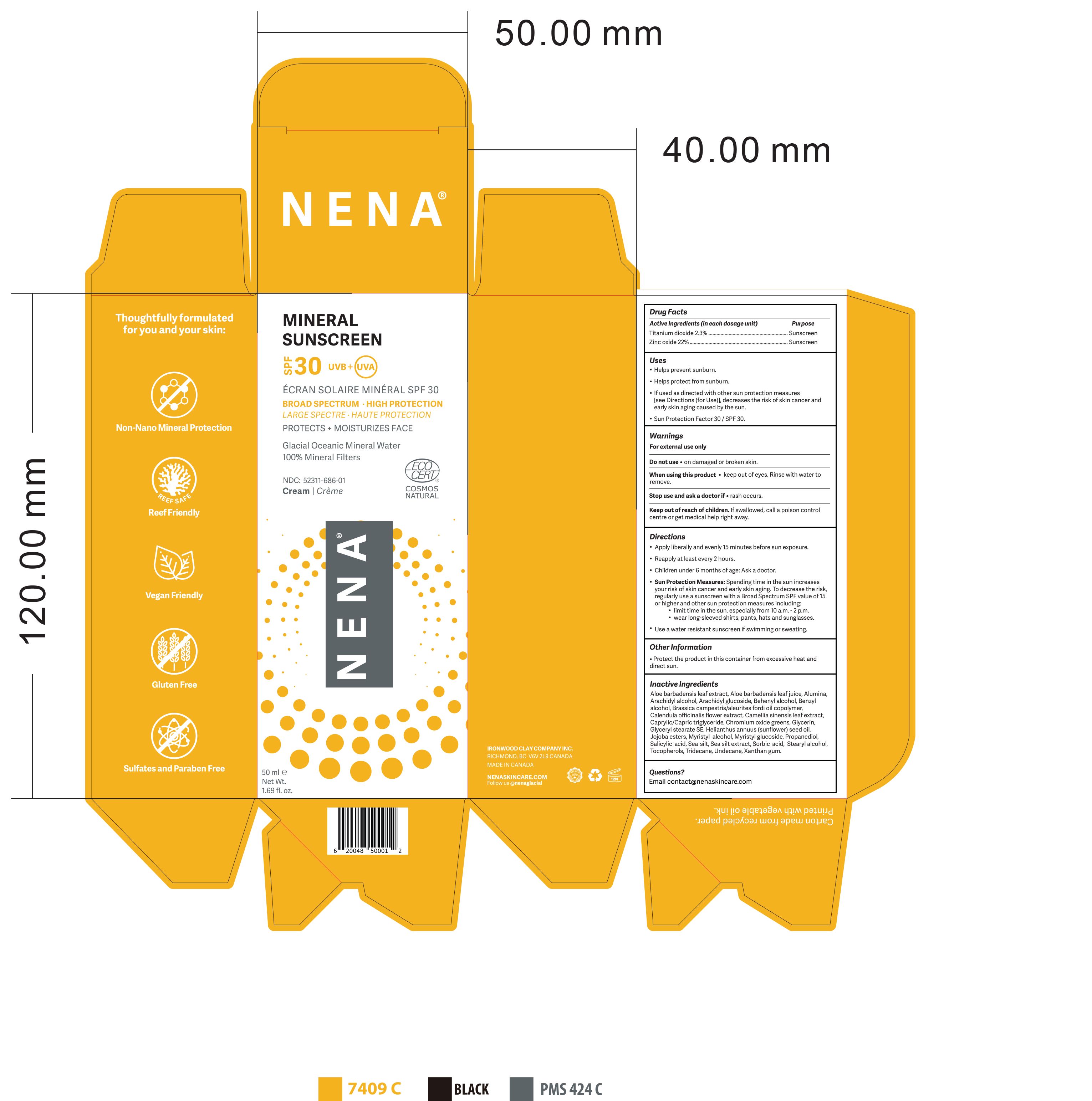 DRUG LABEL: NENA Mineral Sunscreen SPF 30
NDC: 52311-686 | Form: CREAM
Manufacturer: Ironwood Clay Company Inc.
Category: otc | Type: HUMAN OTC DRUG LABEL
Date: 20250409

ACTIVE INGREDIENTS: TITANIUM DIOXIDE 2.3 g/100 mL; ZINC OXIDE 22 g/100 mL
INACTIVE INGREDIENTS: ALUMINUM OXIDE; ALOE VERA LEAF; MEDIUM-CHAIN TRIGLYCERIDES; HYDROGENATED JOJOBA OIL; CALENDULA OFFICINALIS FLOWER; GREEN TEA LEAF; TOCOPHEROL; MYRISTYL GLUCOSIDE; SALICYLIC ACID; PROPANEDIOL; STEARYL ALCOHOL; UNDECANE; XANTHAN GUM; BENZYL ALCOHOL; SORBIC ACID; ARACHIDYL GLUCOSIDE; GLYCERIN; MYRISTYL ALCOHOL; ARACHIDYL ALCOHOL; GLYCERYL STEARATE SE; TRIDECANE; SUNFLOWER OIL; CHROMIC OXIDE; BRASSICA RAPA SUBSP. OLEIFERA WHOLE

Inactive ingredients:

Aloe Barbadensis Leaf Extract
Aloe Barbadensis Leaf Juice
Alumina
Arachidyl Alcohol
Arachidyl Glucoside
Behenyl Alcohol
Benzyl Alcohol
Brassica Campestris/Aleurites Fordi Oil Copolymer
Calendula Officinalis Flower Extract
Camellia Sinensis Leaf Extract
Caprylic/Capric Triglyceride
Chromium Oxide Greens
Glycerin
Glyceryl Stearate SE
Helianthus Annuus (Sunflower) Seed Oil
Jojoba Esters
Myristyl Alcohol
Myristyl Glucoside
Propanediol
Salicylic Acid
Sea Silt
Sea Silt Extract
Sorbic Acid
Stearyl Alcohol,
Tocopherols
Tridecane
Undecane
Xanthan Gum

Warnings

· For external use only
· Do not use • on damaged or broken skin.
· When using this product • keep out of eyes. Rinse with water to remove.
· Stop use and ask a doctor if • rash occurs.
· Keep out of reach of children. If swallowed, call a poison control centre or get medical help right away

Directions

Apply liberally and evenly 15 minutes before sun exposure.
Reapply at least every 2 hours.
Children under 6 months of age: Ask a doctor.
Sun Protection Measures: Spending time in the sun increases your risk of skin cancer and early skin aging. To decrease this risk, regularly use a sunscreen with a Broad Spectrum SPF value of 15 or higher and other sun protection measures including: • limit time in the sun, especially from 10 a.m. - 2 p.m. • wear long-sleeved shirts, pants, hats, and sunglasses.

Use a water resistant sunscreen if swimming or sweating.

Drug Facts

Active ingredients (in each dosage unit) Purpose

Titanium dioxide 2.3% ……………………………………………………………………… Sunscreen

Zinc oxide 22% .…………………….………………………………………………………. Sunscreen

Uses

Helps prevent sunburn.

Helps protect from sunburn.
If used as directed with other sun protection measures [see Directions (for Use)], decreases the risk of skin cancer and early skin aging caused by the sun.
Sun Protection Factor 30 / SPF 30.

Questions?

Email contact@nenaskincare.com

Other information

Protect the product in this container from excessive heat and direct sun.

Dosage: Cream

Route of adminstration: Topical

INDICATIONS AND USAGE

See "Uses" and "Warnings"

KEEP OUT OF REACH OF CHILDREN

Refer to "Keep out of reach of children" in "Warnings" section